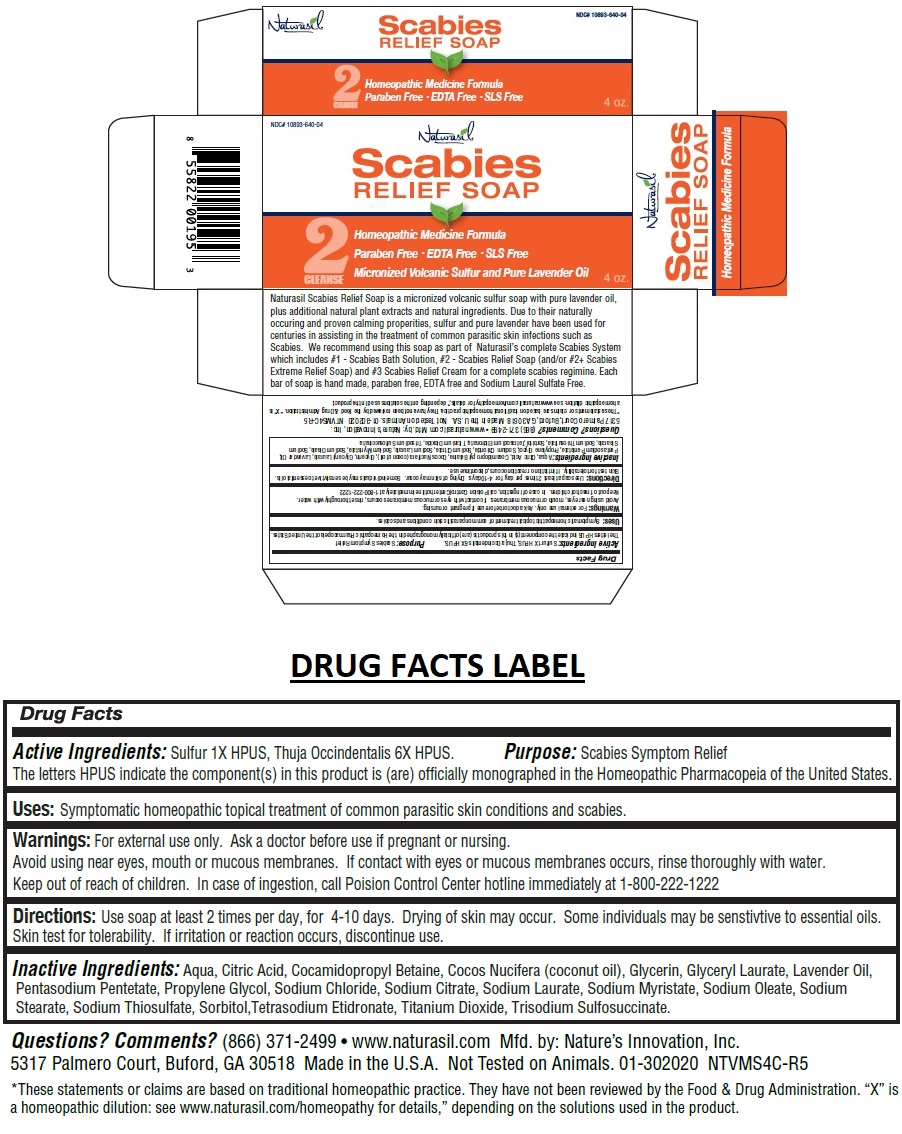 DRUG LABEL: Naturasil
NDC: 10893-640 | Form: SOAP
Manufacturer: Natures Innovation, Inc.
Category: homeopathic | Type: HUMAN OTC DRUG LABEL
Date: 20201022

ACTIVE INGREDIENTS: SULFUR 1 [hp_X]/113.3 g; THUJA OCCIDENTALIS LEAF 6 [hp_X]/113.3 g
INACTIVE INGREDIENTS: WATER; CITRIC ACID MONOHYDRATE; COCAMIDOPROPYL BETAINE; COCONUT OIL; GLYCERIN; GLYCERYL LAURATE; LAVENDER OIL; PENTASODIUM PENTETATE; PROPYLENE GLYCOL; SODIUM CHLORIDE; SODIUM CITRATE, UNSPECIFIED FORM; SODIUM LAURATE; SODIUM MYRISTATE; SODIUM OLEATE; SODIUM STEARATE; SODIUM THIOSULFATE; SORBITOL; ETIDRONATE TETRASODIUM; TITANIUM DIOXIDE; TRISODIUM SULFOSUCCINATE

Naturasil® Scabies RELIEF SOAP

Active Ingredients:

Sulfur 1X HPUS, Thuja Occindentalis 6X HPUS.

The letters HPUS indicate the component(s) in this product is (are) officially monographed in the Homeopathic Pharmacopeia of the United States.

Purpose:

Scabies Symptom Relief

Uses:

Symptomatic homeopathic topical treatment of common parasitic skin conditions and scabies.

Warnings:

For external use only. Ask a doctor before use if pregnant or nursing.
Avoid using near eyes, mouth or mucous membranes. If contact with eyes or mucous membranes occurs, rinse thoroughly with water.

Keep out of reach of children. In case of ingestion, call Poison Control Center hotline immediately at 1-800-222-1222

Directions:

Use soap at least 2 times per day, for 4-10 days. Drying of skin may occur. Some individuals may be sensitive to essential oils.
Skin test for tolerability. If irritation or reaction occurs, discontinue use.

Inactive Ingredients:

Aqua, Citric Acid, Cocamidopropyl Betaine, Cocos Nucifera (coconut oil), Glycerin, Glyceryl Laurate, Lavender Oil, Pentasodium Pentetate, Propylene Glycol, Sodium Chloride, Sodium Citrate, Sodium Laurate, Sodium Myristate, Sodium Oleate, Sodium Stearate, Sodium Thiosulfate, Sorbitol, Tetrasodium Etidronate, Titanium Dioxide, Trisodium Sulfosuccinate.

2 CLEANSE

Homeopathic Medicine Formula

Paraben Free • EDTA Free • SLS Free

Micronized Volcanic Sulfur and Pure Lavender Oil

Naturasil Scabies Relief Soap is a micronized volcanic sulfur soap with pure lavender oil, plus additional natural plant extracts and natural ingredients. Due to their naturally occurring and proven calming properties, sulfur and pure lavender have been used for centuries in assisting in the treatment of common parasitic skin infections such as Scabies. We recommend using this soap as part of Naturasil’s complete Scabies System which includes #1 - Scabies Bath Solution, #2 - Scabies Relief Soap (and/or #2+ Scabies Extreme Relief Soap) and #3 Scabies Relief Cream for a complete scabies regimen. Each bar of soap is hand made, paraben free, EDTA free and Sodium Laurel Sulfate Free.

Questions? Comments? (866) 371-2499 • www.naturasil.com Mfd. by: Nature’s Innovation, Inc.
5317 Palmero Court, Buford, GA 30518 Made in the U.S.A. Not Tested on Animals.
*These statements or claims are based on traditional homeopathic practice. They have not been reviewed by the Food & Drug Administration. “X” is a homeopathic dilution: see www.naturasil.com/homeopathy for details,” depending on the solutions used in the product.